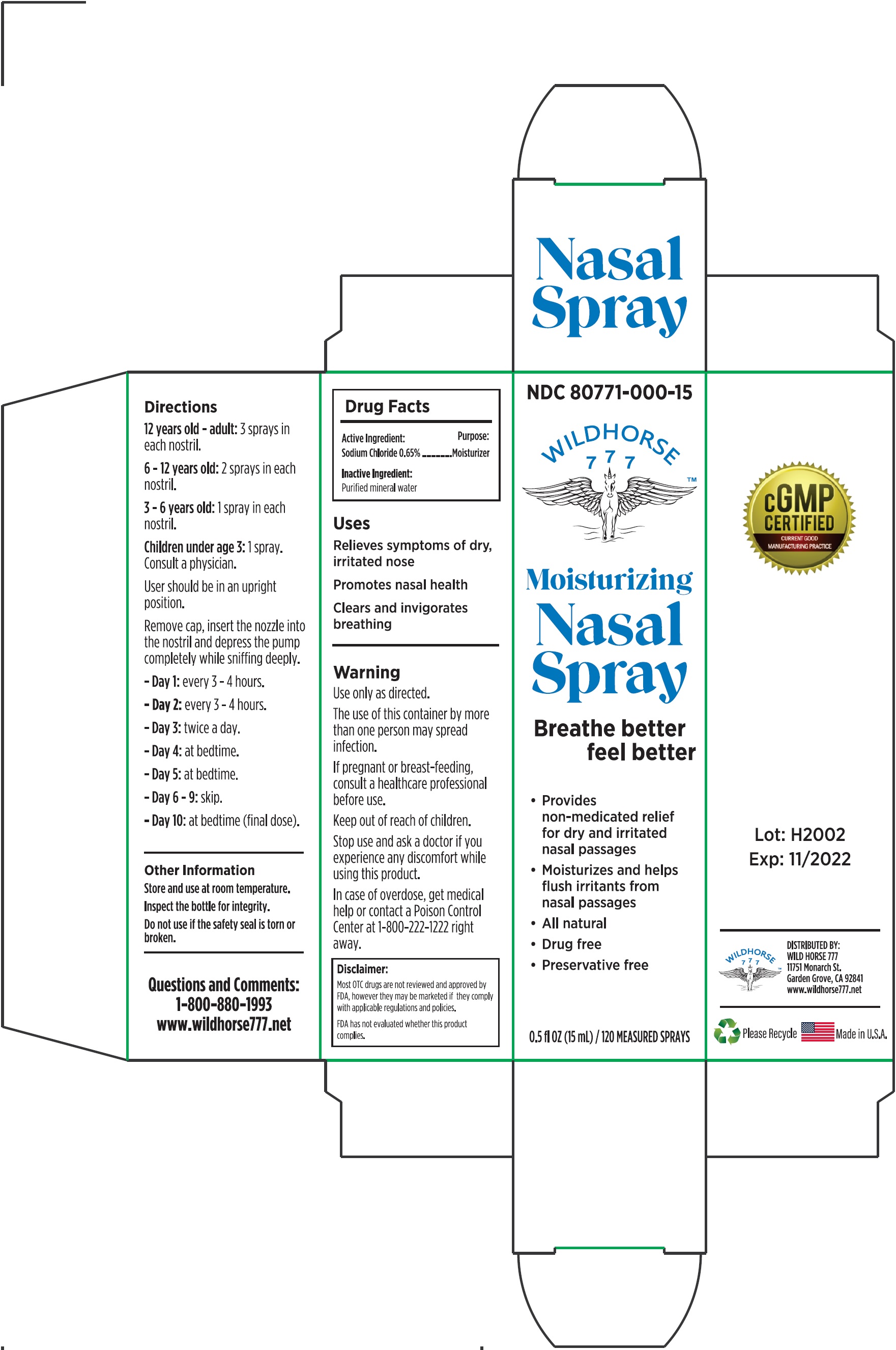 DRUG LABEL: Wild Horse 777 Moisturizing Nasal
NDC: 80771-000 | Form: LIQUID
Manufacturer: Wild Horse 777, Inc.
Category: otc | Type: HUMAN OTC DRUG LABEL
Date: 20220314

ACTIVE INGREDIENTS: SODIUM CHLORIDE 6.5 mg/1 mL
INACTIVE INGREDIENTS: WATER

Wild Horse 777 Moisturizing Nasal Spray

Active Ingredient:

Sodium Chloride 0.65%

Purpose:

Moisturizer

Uses

- Relieves symptoms of dry, irritated nose.

- promotes nasal health.

- Clears and invigorates breathing.

Warnings

- Use only as directed.

- The use of this container by more than one person may spread infection.

If pregnant or breastfeeding,

consult a health care professional before use.

Stop use and ask a doctor

- if you experience any discomfort while using this product.

- In case of overdose, get medical help or contact a Poison Control Center at 1-800-222-1222 right away.

Directions

- 12 years old - adult:3 sprays in each nostril.

- 6-12 years old: 2 sprays in each nostril.

- 2-6 years old: 1 spray in each nostril.

- Children under age 2:1 spray. Consult a physician.

- User should be in an upright position.

- Remove cap, insert the nozzle into the nostril and depress the pump completely while sniffing deeply.

- Day 1: every 3-4 hours.

- Day 2: every 3-4 hours.

- Day 3: twice a day.

- Day 4: at bedtime.

- Day 5: at bedtime.

- Day 6-9: skip.

- Day 10: at bedtime (final dose).

Other Information

- Store and use at room temperature.

- Inspect the bottle for integrity.

- Do not use if the safety seal is torn or broken.

Inactive Ingredient:

Purified mineral water

Questions and Comments:

1-800-880-1993 www.wildhorse777.net